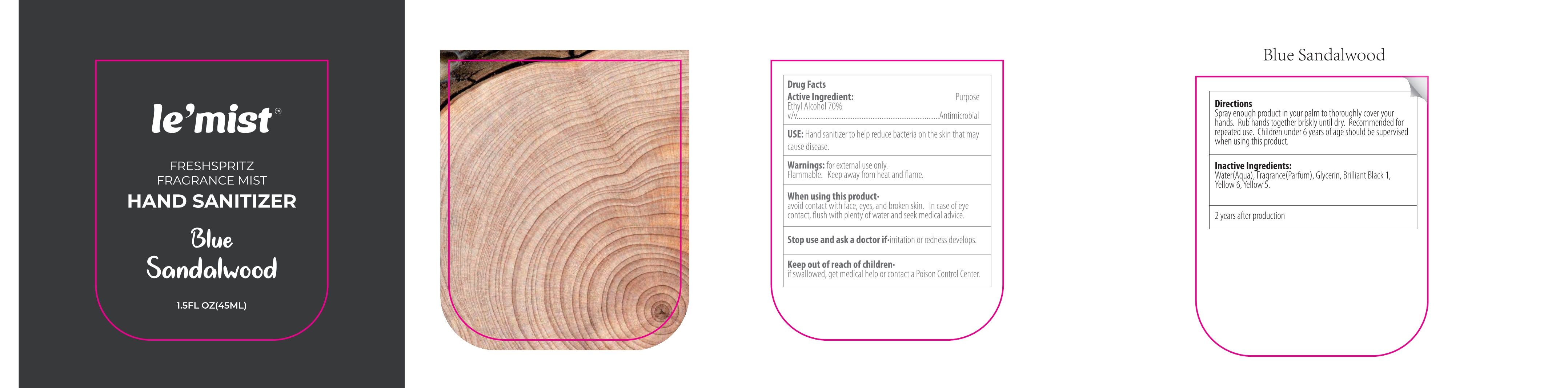 DRUG LABEL: Blue Sandalwood Hand Sanitizer
NDC: 41366-090 | Form: LIQUID
Manufacturer: Zhejiang Meimi Technology Co., Ltd.
Category: otc | Type: HUMAN OTC DRUG LABEL
Date: 20250610

ACTIVE INGREDIENTS: ALCOHOL 70 mL/100 mL
INACTIVE INGREDIENTS: YELLOW 6; GLYCERIN; WATER; YELLOW 5; BRILLIANT BLACK 1

Zhejiang Meimi Technology Co., Ltd.
Blue Sandalwood Hand Sanitizer 45ml
41366-090-01

Active Ingredient(s)

Ethyl Alcohol 70% v/v

Purpose

Antimicrobial

Use

Hand sanitizer to help reduce bacteria on the skin that may cause disease.

Warnings

- for external use only.
- Flammable.
- Keep away from heat and flame.

Stop use and ask a doctor if·irritation or redness develops.

Keep out of reach of children·
if swallowed, get medical help or contact a Poison Control Center.

Directions

Spray enough product in your palm to thoroughly cover your hands. Rub hands together briskly until dry. Recommended for repeated use. Children under 6 years of age should be supervised when using this product.

Inactive ingredients

Water(Aqua), Fragrance(Parfum), Glycerin, Brilliant Black 1, Yellow 6, Yellow 5.

When using this product·
avoid contact with face, eyes, and broken skin. In case of eye contact, flush with plenty of water and seek medical advice.

Package Label - Principal Display Panel

45 mL in 1 BOTTLE

NDC: 41366-090-01